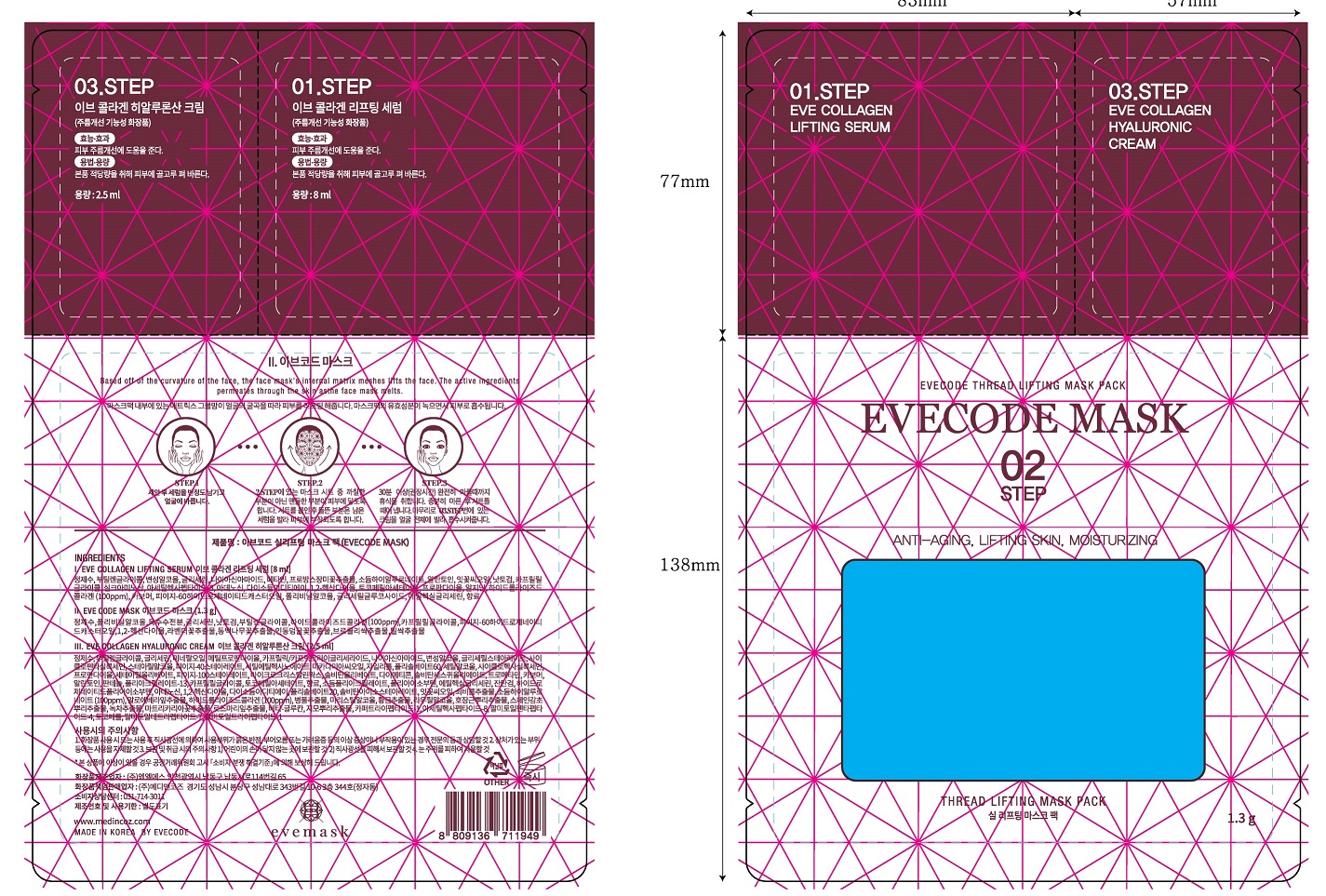 DRUG LABEL: EVECODE THREAD LIFTING MASK PACK
NDC: 73772-0003 | Form: LIQUID
Manufacturer: MEDINCOZ INC.
Category: otc | Type: HUMAN OTC DRUG LABEL
Date: 20200504

ACTIVE INGREDIENTS: NIACINAMIDE 4 g/100 mL
INACTIVE INGREDIENTS: WATER

Drug Facts

ACTIVE INGREDIENT

niacinamide

INACTIVE INGREDIENT

water, glycerin, etc

PURPOSE

wrinkle care

KEEP OUT OF REACH OF THE CHILDREN

INDICATIONS AND USAGE

apply to the face and keep more than 30 minites, and remove

WARNINGS

1) Please consult your doctor if you experience side effects such as swelling, itching, or reddening on the area where you applied the cream.

2) Do not apply on wounds or cuts. 3) Do not store where children may reach, and avoid keeping it exposed to direct sunlight.

DOSAGE AND ADMINISTRATION

external use only